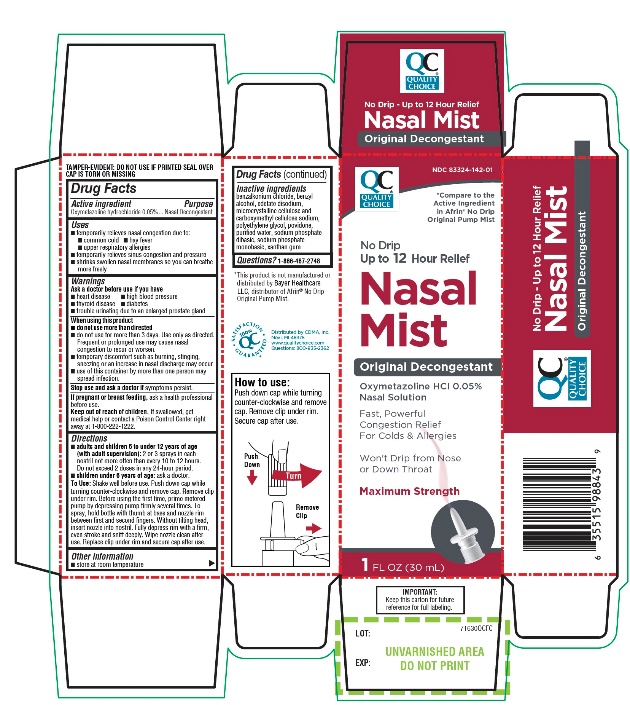 DRUG LABEL: QUALITY CHOICE

NDC: 83324-142 | Form: SPRAY
Manufacturer: QUALITY CHOICE (CHAIN DRUG MARKETING ASSOCIATION)
Category: otc | Type: HUMAN OTC DRUG LABEL
Date: 20250718

ACTIVE INGREDIENTS: OXYMETAZOLINE HYDROCHLORIDE 0.05 g/100 mL
INACTIVE INGREDIENTS: BENZALKONIUM CHLORIDE; BENZYL ALCOHOL; EDETATE DISODIUM; MICROCRYSTALLINE CELLULOSE; CARBOXYMETHYLCELLULOSE SODIUM, UNSPECIFIED; POLYETHYLENE GLYCOL, UNSPECIFIED; POVIDONE, UNSPECIFIED; WATER; SODIUM PHOSPHATE, DIBASIC, UNSPECIFIED FORM; SODIUM PHOSPHATE, MONOBASIC, UNSPECIFIED FORM; XANTHAN GUM

Quality Choice Nasal Mist No Drip Drug Facts

Active ingredient

Oxymetazoline hydrochloride 0.05%

Purpose

Nasal decongestant

Uses

- temporarily relieves nasal congestion due to:
  - common cold
  - hay fever
  - upper respiratory allergies
- temporarily relieves sinus congestion and pressure
- shrinks swollen nasal membranes so you can breathe more freely

Ask a doctor before use if you have

- heart disease
- high blood pressure
- thyroid disease
- diabetes
- trouble urinating due to an enlarged prostate gland

When using this product

- do not use more than directed
- do not use for more than 3 days. Use only as directed. Frequent or prolonged use may cause nasal congestion to recur or worsen.
- temporary discomfort such as burning, stinging, sneezing or an increase in nasal discharge may occur
- use of this container by more than one person may spread infection

Stop use and ask a doctor if

symptoms persist

If pregnant or breast-feeding,

ask a health professional before use.

Keep out of reach of children.

If swallowed, get medical help or contact a Poison Control Center right away at 1-800-222-1222.

Directions

- adults and children 6 to under 12 years of age (with adult supervision):2 or 3 sprays in each nostril not more often than every 10 to 12 hours. Do not exceed 2 doses in any 24-hour period.
- children under 6 years of age:ask a doctor

To Use:Shake well before use. Push down cap while turning counter-clockwise and remove cap. Remove clip under rim. Before using the first time, prime metered pump by depressing pump firmly several times. To spray, hold bottle with thumb at base and nozzle between first and second fingers. Without tilting head, insert nozzle into nostril. Fully depress rim with a firm, even stroke and sniff deeply. Wipe nozzle clean after use. Replace clip under rim and secure cap after use.

Other information

- store at room temperature

TAMPER-EVIDENT: DO NOT USE IF PRINTED SEAL OVER CAP IS TORN OR MISSING

How to use:

Push down cap while turning counter-clockwise and remove cap. Remove clip under rim. Secure cap after use.

Inactive ingredients

benzalkonium chloride, benzyl alcohol, edetate disodium, microcrystalline cellulose and carboxymethylcellulose sodium, polyethylene glycol, povidone, purified water, sodium phosphate dibasic, sodium phosphate monobasic, xanthan gum.

Package/Label Principal Display Panel

QUALITY CHOICE®

NDC 83324-142-01

*Compare to the Active Ingredient in Afrin® No Drip Original Pump Mist

No Drip

Up to 12 Hour Relief

Nasal Mist

Original Decongestant

Oxymetazoline HCl 0.05%

Nasal Solution

Fast, Powerful Congestion Relief

For Colds & Allergies

Won’t Drip from Nose or Down Throat

Maximum Strength

1 FL OZ (30mL)

IMPORTANT:Keep the carton for future reference for full labeling.

100% QC SATISFACTION GURANTEED

Distributed by C.D.M.A., Inc.

Novi, MI 48375

www.qualitychoice.com

Questions: 800-935-2362

*This product is not manufactured or distributed by Bayer Healthcare LLC, distributor of Afrin®No Drip Original Pump Mist.